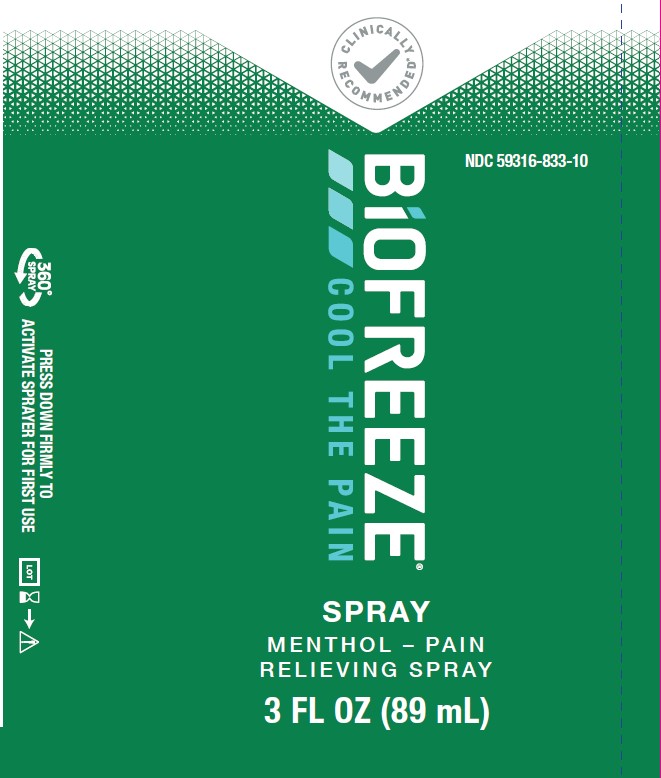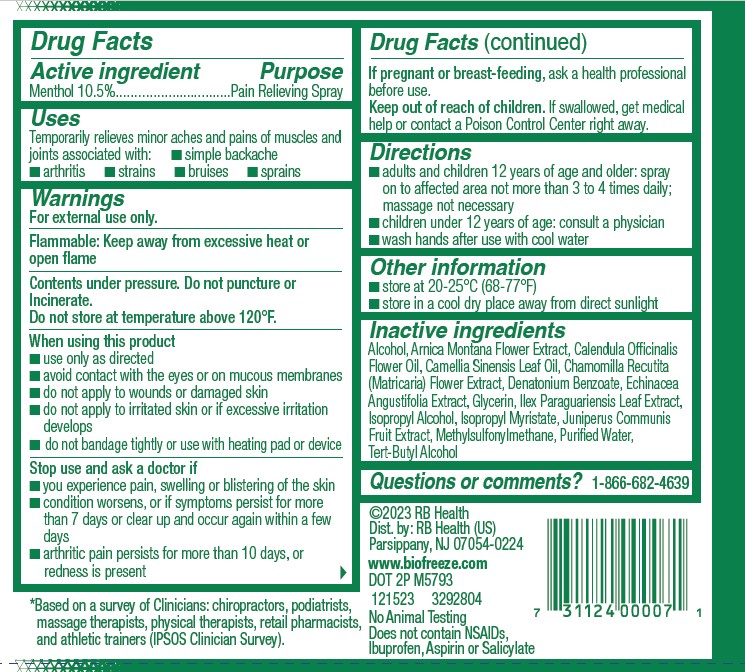 DRUG LABEL: Biofreeze
NDC: 59316-833 | Form: SPRAY
Manufacturer: RB Health (US) LLC
Category: otc | Type: HUMAN OTC DRUG LABEL
Date: 20250902

ACTIVE INGREDIENTS: MENTHOL 105 mg/1 mL
INACTIVE INGREDIENTS: ISOPROPYL ALCOHOL; DENATONIUM BENZOATE; TERT-BUTYL ALCOHOL; ARNICA MONTANA FLOWER; CALENDULA OFFICINALIS FLOWER; CHAMOMILE; DIMETHYL SULFONE; ALCOHOL; ILEX PARAGUARIENSIS LEAF; ISOPROPYL MYRISTATE; JUNIPER BERRY; WATER; ECHINACEA ANGUSTIFOLIA WHOLE; TEA LEAF OIL; GLYCERIN

Biofreeze Spray

Active Ingredients:

Menthol 10.5%

Purpose:

Cooling Pain Relief

Uses

Temporary relief from minor aches and pains of sore muscles and joints associated with: arthritis backache strains and sprains

Warnings

For external use only.

Flammable:

Keep away from excessive heat or open flame.

Contents Under Pressure. Do Not Punture Or Incinerate Do Not Store At Temperature Above 120°F

Ask a Doctor Before using If You have:

■ you experience pain, swelling or blistering of the skin
■ condition worsens, or if symptoms persist for more
than 7 days or clear up and occur again within a few
days
■ arthritic pain persists for more than 10 days, or
redness is present

When Using This Product

Avoid contact with the eyes or mucous membranes; Do not apply to wounds or damaged skin; Do not use with other ointments, creams, sprays or liniments; Do not apply to irritated skin or if excessive irritation develops; Do not bandage; Wash hands after use with cool water; Do not use with heating pad or device; Store in a cool dry place

Stop Use And Ask A Doctor If:

Condition worsens, or if symptoms persist for more than 7 days, or clear up and recur

If pregnant or breast-feeding:

Ask a health professional before use

Keep out of reach of children:

If accidentally ingested, get medical help or contact a Poison Control Center immediately

Directions:

Adults and children 12 years of age and older:Spray on to the affected areas not more than 4 times daily; massage not necessary
Children under 12 years of age:Consult physician

Inactive Ingredients

Alcohol, Arnica Montana Flower Extract, Calendula Officinalis
Flower Oil, Camellia Sinensis Leaf Oil, Chamomilla Recutita
(Matricaria) Flower Extract, Denatonium Benzoate, Echinacea
Angustifolia Extract, Glycerin, Ilex Paraguariensis Leaf Extract,
Isopropyl Alcohol, Isopropyl Myristate, Juniperus Communis
Fruit Extract, Methylsulfonylmethane, Purified Water,
Tert-Butyl Alcohol

Questions or Comments:

1-800-246-3733